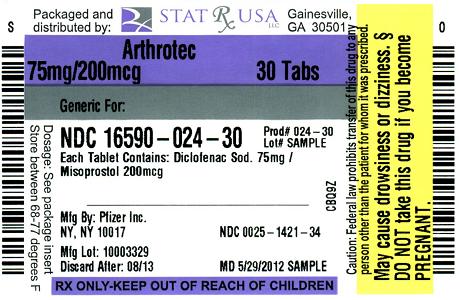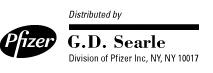 DRUG LABEL: ARTHROTEC
NDC: 16590-024 | Form: TABLET, FILM COATED
Manufacturer: STAT Rx USA LLC
Category: prescription | Type: HUMAN PRESCRIPTION DRUG LABEL
Date: 20120613

ACTIVE INGREDIENTS: DICLOFENAC SODIUM 75 mg/1 1; MISOPROSTOL 200 ug/1 1
INACTIVE INGREDIENTS: SILICON DIOXIDE; CROSPOVIDONE; HYDROGENATED CASTOR OIL; HYPROMELLOSES; LACTOSE; MAGNESIUM STEARATE; CELLULOSE, MICROCRYSTALLINE; POVIDONE K30; SODIUM HYDROXIDE; STARCH, CORN; TALC; TRIETHYL CITRATE

ARTHROTEC®
(diclofenac sodium/misoprostol) Tablets

CONTRAINDICATIONS AND WARNINGS

ARTHROTEC® CONTAINS DICLOFENAC SODIUM AND MISOPROSTOL. ADMINISTRATION OF MISOPROSTOL TO WOMEN WHO ARE PREGNANT CAN CAUSE ABORTION, PREMATURE BIRTH, OR BIRTH DEFECTS. UTERINE RUPTURE HAS BEEN REPORTED WHEN MISOPROSTOL WAS ADMINISTERED IN PREGNANT WOMEN TO INDUCE LABOR OR TO INDUCE ABORTION BEYOND THE EIGHTH WEEK OF PREGNANCY (see also PRECAUTIONS). ARTHROTEC SHOULD NOT BE TAKEN BY PREGNANT WOMEN (see CONTRAINDICATIONS, WARNINGS and PRECAUTIONS).

PATIENTS MUST BE ADVISED OF THE ABORTIFACIENT PROPERTY AND WARNED NOT TO GIVE THE DRUG TO OTHERS. ARTHROTEC should not be used in women of childbearing potential unless the patient requires nonsteroidal anti-inflammatory drug (NSAID) therapy and is at high risk of developing gastric or duodenal ulceration or for developing complications from gastric or duodenal ulcers associated with the use of the NSAID (see WARNINGS). In such patients, ARTHROTEC may be prescribed if the patient:

- has had a negative serum pregnancy test within 2 weeks prior to beginning therapy.
- is capable of complying with effective contraceptive measures.
- has received both oral and written warnings of the hazards of misoprostol, the risk of possible contraception failure, and the danger to other women of childbearing potential should the drug be taken by mistake.
- will begin ARTHROTEC only on the second or third day of the next normal menstrual period.

Cardiovascular Risk

- NSAIDs may cause an increased risk of serious cardiovascular thrombotic events, myocardial infarction, and stroke, which can be fatal. This risk may increase with duration of use. Patients with cardiovascular disease or risk factors for cardiovascular disease may be at greater risk (see WARNINGS).
- ARTHROTEC is contraindicated for treatment of peri-operative pain in the setting of coronary artery bypass graft (CABG) surgery (see WARNINGS).

Gastrointestinal Risk

- NSAIDs cause an increased risk of serious gastrointestinal adverse events including bleeding, ulceration, and perforation of the stomach or intestines, which can be fatal. These events can occur at any time during use and without warning symptoms. Elderly patients are at greater risk for serious gastrointestinal events (see WARNINGS).

DESCRIPTION

ARTHROTEC (diclofenac sodium/misoprostol) is a combination product containing diclofenac sodium, a nonsteroidal anti-inflammatory drug (NSAID) with analgesic properties, and misoprostol, a gastrointestinal (GI) mucosal protective prostaglandin E1 analog. ARTHROTEC oral tablets are white to off-white, round, biconvex, and approximately 11 mm in diameter. Each tablet consists of an enteric-coated core containing 50 mg (ARTHROTEC 50) or 75 mg (ARTHROTEC 75) diclofenac sodium surrounded by an outer mantle containing 200 mcg misoprostol.

Diclofenac sodium is a phenylacetic acid derivative that is a white to off-white, virtually odorless, crystalline powder. Diclofenac sodium is freely soluble in methanol, soluble in ethanol, and practically insoluble in chloroform and in dilute acid. Diclofenac sodium is sparingly soluble in water. Its chemical formula and name are:

C14H10Cl2NO2Na [M.W. = 318.14] 2-[(2,6-dichlorophenyl) amino] benzeneacetic acid, monosodium salt.

Misoprostol is a water-soluble, viscous liquid that contains approximately equal amounts of two diastereomers. Its chemical formula and name are:

C22H38O5 [M.W. = 382.54] (±) methyl 11α,16-dihydroxy-16-methyl-9-oxoprost-13E-en-1-oate.

Inactive ingredients in ARTHROTEC include: colloidal silicon dioxide; crospovidone; hydrogenated castor oil; hypromellose; lactose; magnesium stearate; methacrylic acid copolymer; microcrystalline cellulose; povidone (polyvidone) K-30; sodium hydroxide; starch (corn); talc; triethyl citrate.

CLINICAL PHARMACOLOGY

Pharmacodynamics and pharmacokinetics of diclofenac sodium

Diclofenac sodium is a nonsteroidal anti-inflammatory drug (NSAID). In pharmacologic studies, diclofenac sodium has shown anti-inflammatory, analgesic, and antipyretic properties. The mechanism of action of diclofenac sodium, like other NSAIDs, is not completely understood but may be related to prostaglandin synthetase inhibition.

Diclofenac sodium is completely absorbed from the GI tract after fasting, oral administration. The diclofenac sodium in ARTHROTEC is in a pharmaceutical formulation that resists dissolution in the low pH of gastric fluid but allows a rapid release of drug in the higher pH environment of the duodenum. Only 50% of the absorbed dose is systemically available due to first pass metabolism. Peak plasma levels are achieved in 2 hours (range 1–4 hours), and the area under the plasma concentration curve (AUC) is dose-proportional within the range of 25 mg to 150 mg. Peak plasma levels are less than dose-proportional and are approximately 1.5 and 2.0 mcg/mL for 50 mg and 75 mg doses, respectively.

Five diclofenac metabolites have been identified in human plasma and urine. The metabolites include 4'hydroxy-, 5-hydroxy-, 3'-hydroxy-, 4',5-dihydroxy- and 3'-hydroxy-4'-methoxy diclofenac. The major diclofenac metabolite, 4'-hydroxy-diclofenac, has very weak pharmacologic activity. The formation of 4'-hydroxy diclofenac is primarily mediated by CYP2C9. Both diclofenac and its oxidative metabolites undergo glucuronidation or sulfation followed by biliary excretion. Acylglucuronidation mediated by UGT2B7 and oxidation mediated by CYP2C8 may also play a role in diclofenac metabolism. CYP3A4 is responsible for the formation of minor metabolites, 5-hydroxy and 3'-hydroxy-diclofenac.

Plasma concentrations of diclofenac sodium decline from peak levels in a biexponential fashion, with the terminal phase having a half-life of approximately 2 hours. Clearance and volume of distribution are about 350 mL/min and 550 mL/kg, respectively. More than 99% of diclofenac sodium is reversibly bound to human plasma albumin.

Diclofenac sodium is eliminated through metabolism and subsequent urinary and biliary excretion of the glucuronide and the sulfate conjugates of the metabolites. Approximately 65% of the dose is excreted in the urine and 35% in the bile.

Conjugates of unchanged diclofenac account for 5–10% of the dose excreted in the urine and for less than 5% excreted in the bile. Little or no unchanged unconjugated drug is excreted. Conjugates of the principal metabolite account for 20–30% of the dose excreted in the urine and for 10–20% of the dose excreted in the bile.

Conjugates of three other metabolites together account for 10–20% of the dose excreted in the urine and for small amounts excreted in the bile. The elimination half-life values for these metabolites are shorter than those for the parent drug. Urinary excretion of an additional metabolite (half-life = 80 hours) accounts for only 1.4% of the oral dose. The degree of accumulation of diclofenac metabolites is unknown. Some of the metabolites may have activity.

Pharmacodynamics and pharmacokinetics of misoprostol

Misoprostol is a synthetic prostaglandin E1 analog with gastric antisecretory and (in animals) mucosal protective properties. NSAIDs inhibit prostaglandin synthesis. A deficiency of prostaglandins within the gastric and duodenal mucosa may lead to diminishing bicarbonate and mucus secretion and may contribute to the mucosal damage caused by NSAIDs.

Misoprostol can increase bicarbonate and mucus production, but in humans this has been shown at doses 200 mcg and above that are also antisecretory. It is therefore not possible to tell whether the ability of misoprostol to reduce the risk of gastric and duodenal ulcers is the result of its antisecretory effect, its mucosal protective effect, or both.

In vitro studies on canine parietal cells using titrated misoprostol acid as the ligand have led to the identification and characterization of specific prostaglandin receptors. Receptor binding is saturable, reversible, and stereo-specific. The sites have a high affinity for misoprostol, for its acid metabolite, and for other E type prostaglandins, but not for F or I prostaglandins and other unrelated compounds, such as histamine or cimetidine. Receptor-site affinity for misoprostol correlates well with an indirect index of antisecretory activity. It is likely that these specific receptors allow misoprostol taken with food to be effective topically, despite the lower serum concentrations attained.

Misoprostol produces a moderate decrease in pepsin concentration during basal conditions, but not during histamine stimulation. It has no significant effect on fasting or postprandial gastrin nor intrinsic factor output.

Effects on gastric acid secretion

Misoprostol, over the range of 50–200 mcg, inhibits basal and nocturnal gastric acid secretion, and acid secretion in response to a variety of stimuli, including meals, histamine, pentagastrin, and coffee. Activity is apparent 30 minutes after oral administration and persists for at least 3 hours. In general, the effects of 50 mcg were modest and shorter-lived, and only the 200 mcg dose had substantial effects on nocturnal secretion or on histamine- and meal-stimulated secretion.

Orally administered misoprostol is rapidly and extensively absorbed, and it undergoes rapid metabolism to its biologically active metabolite, misoprostol acid. Misoprostol acid in ARTHROTEC reaches a maximum plasma concentration in about 20 minutes and is, thereafter, quickly eliminated with an elimination t1/2 of about 30 minutes. There is high variability in plasma levels of misoprostol acid between and within studies, but mean values after single doses show a linear relationship with dose of misoprostol over the range of 200 to 400 mcg. No accumulation of misoprostol acid was found in multiple-dose studies, and plasma steady state was achieved within 2 days. The serum protein binding of misoprostol acid is less than 90% and is concentration-independent in the therapeutic range.

After oral administration of radio-labeled misoprostol, about 70% of detected radioactivity appears in the urine. Maximum plasma concentrations of misoprostol acid are diminished when the dose is taken with food, and total availability of misoprostol acid is reduced by use of concomitant antacid. Clinical trials were conducted with concomitant antacid; this effect does not appear to be clinically important.

Pharmacokinetic studies also showed a lack of drug interaction with antipyrine or propranolol given with misoprostol. Misoprostol given for 1 week had no effect on the steady state pharmacokinetics of diazepam when the two drugs were administered 2 hours apart.

Pharmacokinetics of ARTHROTEC

The pharmacokinetics following oral administration of a single dose (see Table 1) or multiple doses of ARTHROTEC (diclofenac sodium/misoprostol) to healthy subjects under fasted conditions are similar to the pharmacokinetics of the two individual components.

Table 1
MISOPROSTOL ACID Mean (SD)
Treatment (n=36) | Cmax (pg/mL) | tmax (hr) | AUC (0–4h) (pg∙hr/mL)
ARTHROTEC 50 | 441 (137) | 0.30 (0.13) | 266 (95)
Cytotec® | 478 (201) | 0.30 (0.10) | 295 (143)
ARTHROTEC 75 | 304 (110) | 0.26 (0.09) | 177 (49)
Cytotec | 290 (130) | 0.35 (0.12) | 176 (58)
DICLOFENAC Mean (SD)
Treatment (n=36) | Cmax (ng/mL) | tmax (hr) | AUC (0–12h) (ng∙hr/mL)
ARTHROTEC 50 | 1207 (364) | 2.4 (1.0) | 1380 (272)
Voltaren® | 1298 (441) | 2.4 (1.0) | 1357 (290)
ARTHROTEC 75 | 2025 (2005) | 2.0 (1.4) | 2773 (1347)
Voltaren | 2367 (1318) | 1.9 (0.7) | 2609 (1185)
SD: Standard deviation of the mean
AUC: Area under the curve
Cmax: Peak concentration
tmax: Time to peak concentration

The rate and extent of absorption of both diclofenac sodium and misoprostol acid from ARTHROTEC 50 and ARTHROTEC 75 are similar to those from diclofenac sodium and misoprostol formulations each administered alone.

Neither diclofenac sodium nor misoprostol acid accumulated in plasma following repeated doses of ARTHROTEC given every 12 hours under fasted conditions. Food decreases the multiple-dose bioavailability profile of ARTHROTEC 50 and ARTHROTEC 75.

Specific populations

A 4-week study, comparing plasma level profiles of diclofenac (50 mg bid) in younger (26–46 years) versus older (66–81 years) adults, did not show differences between age groups (10 patients per age group). In a multiple-dose (bid) crossover study of 24 people aged 65 years or older, the misoprostol contained in ARTHROTEC did not affect the pharmacokinetics of diclofenac sodium.

Differences in the pharmacokinetics of diclofenac have not been detected in studies of patients with renal (50 mg intravenously) or hepatic impairment (100 mg oral solution). In patients with renal impairment (N=5, creatinine clearance 3 to 42 mL/min), AUC values and elimination rates were comparable to those in healthy people. In patients with biopsy-confirmed cirrhosis or chronic active hepatitis (variably elevated transaminases and mildly elevated bilirubins, N=10), diclofenac concentrations and urinary elimination values were comparable to those in healthy people.

Pharmacokinetic studies with misoprostol in patients with varying degrees of renal impairment showed an approximate doubling of t1/2, Cmax, and AUC compared to healthy people. In people over 64 years of age, the AUC for misoprostol acid is increased.

In a study of people with mild to moderate hepatic impairment, mean misoprostol acid AUC and Cmax showed approximately double the mean values obtained in healthy people. Three people who had the lowest antipyrine and lowest indocyanine green clearance values had the highest misoprostol acid AUC and Cmax values.

After a single oral dose of misoprostol to nursing mothers, misoprostol acid was excreted in breast milk. The maximum concentration of misoprostol acid in expressed breast milk was achieved within 1 hour after dosing and was 7.6 pg/mL (CV 37%) and 20.9 pg/mL (CV 77%) after single 200 µg and 600 µg misoprostol administration, respectively. The misoprostol acid concentrations in breast milk declined to < 1 pg/mL at 5 hours post-dose.

CLINICAL STUDIES

Osteoarthritis

Diclofenac sodium, as a single ingredient or in combination with misoprostol, has been shown to be effective in the management of the signs and symptoms of osteoarthritis.

Rheumatoid arthritis

Diclofenac sodium, as a single ingredient or in combination with misoprostol, has been shown to be effective in the management of the signs and symptoms of rheumatoid arthritis.

Upper gastrointestinal safety

Diclofenac, and other NSAIDs, have caused serious gastrointestinal toxicity, such as bleeding, ulceration, and perforation of the stomach, small intestine or large intestine. Misoprostol has been shown to reduce the incidence of endoscopically diagnosed NSAID-induced gastric and duodenal ulcers. In a 12-week, randomized, double-blind, dose-response study, misoprostol 200 mcg administered qid, tid, or bid, was significantly more effective than placebo in reducing the incidence of gastric ulcer in OA and RA patients using a variety of NSAIDs. The tid regimen was therapeutically equivalent to misoprostol 200 mcg qid with respect to the prevention of gastric ulcers. Misoprostol 200 mcg given bid was less effective than 200 mcg given tid or qid. The incidence of NSAID-induced duodenal ulcer was also significantly reduced with all three regimens of misoprostol compared to placebo (see Table 2).

Table 2
Misoprostol 200 mcg Dosage Regimen
 | Placebo | bid | tid | qid
Gastric ulcer | 11% | 6% [Misoprostol significantly different from placebo (p<0.05)] | 3% | 3%
Duodenal ulcer | 6% | 2% | 3% | 1%
N=1623; 12 weeks

Results of a study in 572 patients with osteoarthritis demonstrate that patients receiving ARTHROTEC have a lower incidence of endoscopically defined gastric ulcers compared to patients receiving diclofenac sodium (see Table 3).

Table 3
Osteoarthritis patients with history of ulcer or erosive disease (N=572), 6 weeks | Incidence of ulcers
Osteoarthritis patients with history of ulcer or erosive disease (N=572), 6 weeks | Gastric | Duodenal
ARTHROTEC 50 tid | 3% [Statistically significantly different from diclofenac (p<0.05)] | 6%
ARTHROTEC 75 bid | 4% | 3%
diclofenac sodium 75 mg bid | 11% | 7%
placebo | 3% | 1%

INDICATIONS AND USAGE

Carefully consider the potential benefits and risks of ARTHROTEC and other treatment options before deciding to use ARTHROTEC. Use the lowest effective dose for the shortest duration consistent with individual patient treatment goals (see WARNINGS).

ARTHROTEC is indicated for treatment of the signs and symptoms of osteoarthritis or rheumatoid arthritis in patients at high risk of developing NSAID-induced gastric and duodenal ulcers and their complications. See WARNINGS, Gastrointestinal Effects - Risk of Ulceration, Bleeding, and Perforation for a list of factors that may increase the risk of NSAID-induced gastric and duodenal ulcers and their complications.

CONTRAINDICATIONS

See boxed CONTRAINDICATIONS AND WARNINGS related to misoprostol.

ARTHROTEC should not be taken by pregnant women.

ARTHROTEC is contraindicated in patients with hypersensitivity to diclofenac or to misoprostol or other prostaglandins. ARTHROTEC should not be given to patients who have experienced asthma, urticaria, or other allergic-type reactions after taking aspirin or other NSAIDs. Severe, rarely fatal, anaphylactic-like reactions to diclofenac sodium have been reported in such patients (see WARNINGS- Anaphylactic Reactions, and PRECAUTIONS- Preexisting Asthma).

ARTHROTEC is contraindicated for the treatment of peri-operative pain in the setting of coronary artery bypass graft (CABG) surgery (see boxed CONTRAINDICATIONS AND WARNINGS).

WARNINGS

Regarding misoprostol:

See boxed CONTRAINDICATIONS AND WARNINGS.

Regarding diclofenac:

See boxed CONTRAINDICATIONS AND WARNINGS.

CARDIOVASCULAR EFFECTS

Cardiovascular Thrombotic Events

Clinical trials of several COX-2 selective and nonselective NSAIDs of up to three years duration have shown an increased risk of serious cardiovascular (CV) thrombotic events, myocardial infarction, and stroke, which can be fatal. All NSAIDs, both COX-2 selective and nonselective, may have a similar risk. Patients with known CV disease or risk factors for CV disease may be at greater risk. To minimize the potential risk for an adverse CV event in patients treated with an NSAID, the lowest effective dose should be used for the shortest duration possible. Physicians and patients should remain alert for the development of such events, even in the absence of previous CV symptoms. Patients should be informed about the signs and/or symptoms of serious CV events and the steps to take if they occur.

There is no consistent evidence that concurrent use of aspirin mitigates the increased risk of serious CV thrombotic events associated with NSAID use. The concurrent use of aspirin and an NSAID does increase the risk of serious GI events (see WARNINGS, Gastrointestinal Effects - Risk of Ulceration, Bleeding, and Perforation).

Two large, controlled clinical trials of a COX-2 selective NSAID for the treatment of pain in the first 10–14 days following CABG surgery found an increased incidence of myocardial infarction and stroke (see CONTRAINDICATIONS).

Hypertension

NSAIDs, including ARTHROTEC, can lead to onset of new hypertension or worsening of preexisting hypertension, either of which may contribute to the increased incidence of CV events. Patients taking thiazides or loop diuretics may have impaired response to these therapies when taking NSAIDs. NSAIDs, including ARTHROTEC, should be used with caution in patients with hypertension. Blood pressure (BP) should be monitored closely during the initiation of NSAID treatment and throughout the course of therapy.

Congestive Heart Failure and Edema

Fluid retention and edema have been observed in some patients taking NSAIDs. ARTHROTEC should be used with caution in patients with fluid retention or heart failure.

Gastrointestinal Effects - Risk of Ulceration, Bleeding, and Perforation

NSAIDs, including ARTHROTEC, can cause serious gastrointestinal (GI) adverse events including inflammation, bleeding, ulceration, and perforation of the stomach, small intestine, or large intestine, which can be fatal. These serious adverse events can occur at any time, with or without warning symptoms, in patients treated with NSAIDs. Only one in five patients who develop a serious upper GI adverse event on NSAID therapy is symptomatic. Upper GI ulcers, gross bleeding, or perforation caused by NSAIDs occur in approximately 1% of patients treated for 3–6 months, and in about 2–4% of patients treated for one year. These trends continue with longer duration of use, increasing the likelihood of developing a serious GI event at some time during the course of therapy. However, even short-term therapy is not without risk. NSAIDs should be prescribed with extreme caution in those with a prior history of ulcer disease or gastrointestinal bleeding. Patients with a prior history of peptic ulcer disease and/or gastrointestinal bleeding who use NSAIDs have a greater than 10-fold increased risk for developing a GI bleed compared to patients treated with neither of these risk factors. Other factors that increase the risk of GI bleeding in patients treated with NSAIDs include concomitant use of oral corticosteroids or anticoagulants, longer duration of NSAID therapy, smoking, use of alcohol, older age, and poor general health status. Most spontaneous reports of fatal GI events are in elderly or debilitated patients, and therefore, special care should be taken in treating this population.

To minimize the potential risk for an adverse GI event in patients treated with an NSAID, the lowest effective dose should be used for the shortest possible duration. Patients and physicians should remain alert for signs and symptoms of GI ulcerations and bleeding during NSAID therapy and promptly initiate additional evaluation and treatment if a serious GI event is suspected. This should include discontinuation of the NSAID until a serious GI adverse event is ruled out. For high risk patients, alternate therapies that do not involve NSAIDs should be considered.

Renal Effects

Long-term administration of NSAIDs has resulted in renal papillary necrosis and other renal injury. Renal toxicity has also been seen in patients in whom renal prostaglandins have a compensatory role in the maintenance of renal perfusion. In these patients, administration of a nonsteroidal anti-inflammatory drug may cause a dose-dependent reduction in prostaglandin formation and, secondarily, in renal blood flow, which may precipitate overt renal decompensation. Patients at greatest risk of this reaction are those with impaired renal function, heart failure, liver dysfunction, those taking diuretics and ACE-inhibitors, and the elderly. Discontinuation of NSAID therapy is usually followed by recovery to the pretreatment state.

Advanced Renal Disease

ARTHROTEC contains diclofenac. Diclofenac metabolites are eliminated primarily by the kidneys. The extent to which the metabolites may accumulate in patients with renal failure has not been studied. Therefore, treatment with ARTHROTEC is not recommended in patients with advanced renal disease. If ARTHROTEC therapy must be initiated, close monitoring of the patient's renal function is advisable.

Hepatic Effects

In clinical trials with ARTHROTEC, meaningful elevation of ALT (SGPT, more than 3 times the ULN [ULN = the upper limit of the normal range]) occurred in 1.6% of 2,184 patients treated with ARTHROTEC and in 1.4% of 1,691 patients treated with diclofenac sodium. These increases were generally transient, and enzyme levels returned to within the normal range upon discontinuation of therapy with ARTHROTEC. The misoprostol component of ARTHROTEC does not appear to exacerbate the hepatic effects caused by the diclofenac sodium component.

Elevations of one or more liver tests may occur during therapy with diclofenac, a component of ARTHROTEC. These laboratory abnormalities may progress, may remain unchanged, or may be transient with continued therapy. Borderline elevations (i.e., less than 3 times the ULN), or greater elevations of transaminases occurred in about 15% of diclofenac-treated patients. Of the markers of hepatic function, ALT (SGPT) is recommended for the monitoring of liver injury.

In clinical trials, meaningful elevations (i.e., more than 3 times the ULN) of AST (SGOT) (ALT was not measured in all studies) occurred in about 2% of approximately 5,700 patients at some time during diclofenac treatment. In a large, open-label, controlled trial of 3,700 patients treated for 2–6 months, patients were monitored first at 8 weeks and 1,200 patients were monitored again at 24 weeks. Meaningful elevations of ALT and/or AST occurred in about 4% of patients and included marked elevations (i.e., more than 8 times the ULN) in about 1% of the 3,700 patients. In that open-label study, a higher incidence of borderline (less than 3 times the ULN), moderate (3–8 times the ULN), and marked (>8 times the ULN) elevations of ALT or AST was observed in patients receiving diclofenac when compared to other NSAIDs. Elevations in transaminases were seen more frequently in patients with osteoarthritis than in those with rheumatoid arthritis. In another clinical trial where over 17,000 patients received diclofenac for a mean of 18 months, hepatitis was rarely observed.

Almost all meaningful elevations in transaminases were detected before patients became symptomatic. Abnormal tests occurred during the first 2 months of therapy with diclofenac in 42 of the 51 patients in all trials who developed marked transaminase elevations.

In postmarketing reports, cases of drug-induced hepatotoxicity have been reported in the first month, and usually occur within 1-6 months, but can occur at any time during treatment with diclofenac. Postmarketing surveillance has reported cases of severe hepatic reactions, including liver necrosis, jaundice, fulminant hepatitis with and without jaundice, and liver failure. Some of these reported cases resulted in fatalities or liver transplantation.

Physicians should measure transaminases periodically in patients receiving long-term therapy with diclofenac, because severe hepatotoxicity may develop without a prodrome of distinguishing symptoms. The optimum times for making the first and subsequent transaminase measurements are not known. Based on clinical trial data and postmarketing experiences, transaminases should be monitored within 4 to 8 weeks after initiating treatment with diclofenac. However, severe hepatic reactions can occur at any time during treatment with diclofenac.

If abnormal liver tests persist or worsen, if clinical signs and/or symptoms consistent with liver disease develop, or if systemic manifestations occur (e.g., eosinophilia, rash, abdominal pain, diarrhea, dark urine, etc.), ARTHROTEC should be discontinued immediately.

To minimize the possibility that hepatic injury will become severe between transaminase measurements, physicians should inform patients of the warning signs and symptoms of hepatotoxicity (e.g., nausea, fatigue, lethargy, pruritus, jaundice, right upper quadrant tenderness, and "flu-like" symptoms), and the appropriate action patients should take if these signs and symptoms appear.

To minimize the potential risk for an adverse liver related event in patients treated with ARTHROTEC, the lowest effective dose should be used for the shortest duration possible. Caution should be exercised in prescribing ARTHROTEC with concomitant drugs that are known to be potentially hepatotoxic (e.g., antibiotics, anti-epileptics).

Anaphylactic Reactions

As with other NSAIDs, anaphylactic reactions may occur in patients without known prior exposure to ARTHROTEC. ARTHROTEC should not be given to patients with the aspirin triad. This symptom complex typically occurs in asthmatic patients who experience rhinitis with or without nasal polyps, or who exhibit severe, potentially fatal bronchospasm after taking aspirin or other NSAIDs (see CONTRAINDICATIONS and PRECAUTIONS—Preexisting Asthma). Anaphylactic reactions may also occur to the misoprostol component of ARTHROTEC. Emergency help should be sought in cases where an anaphylactic reaction occurs. Allergic reactions have been reported by less than 0.1% of patients who received ARTHROTEC in clinical trials, and there have been rare reports of anaphylaxis in the marketed use of ARTHROTEC outside of the United States.

Skin Reactions

NSAIDs, including ARTHROTEC, can cause serious skin adverse events such as exfoliative dermatitis, Stevens-Johnson Syndrome (SJS), and toxic epidermal necrolysis (TEN), which can be fatal. These serious events may occur without warning. Patients should be informed about the signs and symptoms of serious skin manifestations and use of drug should be discontinued at the first appearance of skin rash or any other sign of hypersensitivity.

Pregnancy

In late pregnancy, as with other NSAIDs, ARTHROTEC should be avoided because it may cause premature closure of the ductus arteriosus.

PRECAUTIONS

General

ARTHROTEC cannot be expected to substitute for corticosteroids or to treat corticosteroid insufficiency. Abrupt discontinuation of corticosteroids may lead to disease exacerbation. Patients on prolonged corticosteroid therapy should have their therapy tapered slowly if a decision is made to discontinue corticosteroids.

The pharmacological activity of ARTHROTEC in reducing fever and inflammation may diminish the utility of these diagnostic signs in detecting complications of presumed noninfectious, painful conditions.

Hepatic Effects

See WARNINGS.

Hematological Effects

Anemia is sometimes seen in patients receiving NSAIDs, including ARTHROTEC. This may be due to fluid retention, occult or gross GI blood loss, or an incompletely described effect upon erythropoiesis. Patients on long-term treatment with NSAIDs, including ARTHROTEC, should have their hemoglobin or hematocrit checked if they exhibit any signs or symptoms of anemia.

NSAIDs inhibit platelet aggregation and have been shown to prolong bleeding time in some patients. Unlike aspirin, their effect on platelet function is quantitatively less, of shorter duration, and reversible. Patients receiving ARTHROTEC who may be adversely affected by alterations in platelet function, such as those with coagulation disorders or patients receiving anticoagulants, should be carefully monitored.

Preexisting Asthma

Patients with asthma may have aspirin-sensitive asthma. The use of aspirin in patients with aspirin-sensitive asthma has been associated with severe bronchospasm which can be fatal. Since cross reactivity, including bronchospasm, between aspirin and other nonsteroidal anti-inflammatory drugs has been reported in such aspirin-sensitive patients, ARTHROTEC should not be administered to patients with this form of aspirin sensitivity and should be used with caution in patients with preexisting asthma.

Aseptic Meningitis

As with other NSAIDs, aseptic meningitis with fever and coma has been observed on rare occasions in patients on diclofenac therapy. Although it is probably more likely to occur in patients with systemic lupus and related connective tissue diseases, it has been reported in patients who do not have an underlying chronic disease. If signs or symptoms of meningitis develop in a patient on diclofenac, the possibility of it being related to diclofenac should be considered.

Porphyria

The use of ARTHROTEC in patients with hepatic porphyria should be avoided. To date, one patient has been described in whom diclofenac sodium probably triggered a clinical attack of porphyria. The postulated mechanism, demonstrated in rats, for causing such attacks by diclofenac sodium, as well as some other NSAIDs, is through stimulation of the porphyrin precursor delta-aminolevulinic acid (ALA).

Information for patients

Women of childbearing potential using ARTHROTEC to treat arthritis should be told that they must not be pregnant when therapy with ARTHROTEC is initiated, and that they must use an effective contraception method while taking ARTHROTEC. See boxed CONTRAINDICATIONS AND WARNINGS.

THE PATIENT SHOULD NOT GIVE ARTHROTEC TO ANYONE ELSE. ARTHROTEC has been prescribed for the patient's specific condition, may not be the correct treatment for another person, and may be dangerous to the other person if she were to become pregnant.

SPECIAL NOTE FOR WOMEN: ARTHROTEC contains diclofenac sodium and misoprostol. Misoprostol may cause abortion (sometimes incomplete), premature labor, or birth defects if given to pregnant women.

Patients should be informed of the following information before initiating therapy with an NSAID and periodically during the course of ongoing therapy. Patients should also be encouraged to read the NSAID Medication Guide that accompanies each prescription dispensed.

- ARTHROTEC, like other NSAIDs, may cause serious side effects, such as MI or stroke, which may result in hospitalization and even death. Although serious CV events can occur without warning symptoms, patients should be alert for the signs and symptoms of chest pain, shortness of breath, weakness, slurring of speech, and should ask for medical advice when observing any indicative sign or symptoms. Patients should be apprised of the importance of this follow-up (see WARNINGS, CARDIOVASCULAR EFFECTS).
- ARTHROTEC, like other NSAIDs, can cause GI discomfort and, rarely, serious GI side effects, such as ulcers and bleeding, which may result in hospitalization and even death. Although serious GI tract ulcerations and bleeding can occur without warning symptoms, patients should be alert for the signs and symptoms of ulceration and bleeding, and should ask for medical advice when observing any indicative sign or symptoms, including epigastric pain, dyspepsia, melena, and hematemesis. Patients should be apprised of the importance of this follow-up (see WARNINGS, Gastrointestinal Effects - Risk of Ulceration, Bleeding, and Perforation).
- ARTHROTEC, like other NSAIDs, can cause serious skin side effects, such as exfoliative dermatitis, SJS, and TEN, which may result in hospitalization and even death. Although serious skin reactions may occur without warning, patients should be alert for the signs and symptoms of skin rash and blisters, fever, or other signs of hypersensitivity such as itching, and should ask for medical advice when observing any indicative sign or symptoms. Patients should be advised to stop the drug immediately if they develop any type of rash and contact their physicians as soon as possible.
- Patients should promptly report signs or symptoms of unexplained weight gain or edema to their physicians.
- Patients should be informed of the warning signs and symptoms of hepatotoxicity (e.g., nausea, fatigue, lethargy, pruritus, jaundice, right upper quadrant tenderness, and "flu-like" symptoms). If these occur, patients should be instructed to stop therapy and seek immediate medical attention.
- Patients should be informed of the signs of an anaphylactic reaction (e.g., difficulty breathing, swelling of the face or throat). If these occur, patients should be instructed to seek immediate emergency help (see WARNINGS, Anaphylactic Reactions).
- In late pregnancy, as with other NSAIDs, ARTHROTEC should not be taken because it may cause premature closure of the ductus arteriosus.
- ARTHROTEC should not be taken by nursing mothers.
- Concomitant use of voriconazole increases the systemic exposure to diclofenac. When concomitant voriconazole use is necessary, the total daily dose of diclofenac should not exceed the lowest recommended dose of ARTHROTEC 50 twice daily (see Drug Interactions and DOSAGE AND ADMINISTRATION).

See PATIENT INFORMATION at the end of this labeling for important information to discuss with the patient.

ARTHROTEC is available only as a unit-of-use package that includes a leaflet containing patient information. The patient should read the leaflet before taking ARTHROTEC and each time the prescription is renewed because the leaflet may have been revised. Keep ARTHROTEC out of the reach of children.

Laboratory Tests

Because serious GI tract ulcerations and bleeding can occur without warning symptoms, physicians should monitor for signs or symptoms of GI bleeding. Patients on long-term treatment with NSAIDs should have their CBC and a chemistry profile checked periodically. If clinical signs and symptoms consistent with liver or renal disease develop, systemic manifestations occur (e.g., eosinophilia, rash, etc.), or if abnormal liver tests persist or worsen, ARTHROTEC should be discontinued.

Effect on blood coagulation

Diclofenac sodium impairs platelet aggregation but does not affect bleeding time, plasma thrombin clotting time, plasma fibrinogen, or factors V and VII to XII. Statistically significant changes in prothrombin and partial thromboplastin times have been reported in normal volunteers. The mean changes were observed to be less than 1 second in both instances, however, and are unlikely to be clinically important. Diclofenac sodium is a prostaglandin synthetase inhibitor, however, and all drugs that inhibit prostaglandin synthesis interfere with platelet function to some degree; therefore, patients who may be adversely affected by such an action should be carefully observed. Misoprostol has not been shown to exacerbate the effects of diclofenac on platelet activity.

Drug Interactions

ACE-Inhibitors

Reports suggest that NSAIDs may diminish the antihypertensive effect of ACE-inhibitors. This interaction should be given consideration in patients taking NSAIDs concomitantly with ACE-inhibitors.

In patients who are elderly, volume-depleted (including those on diuretic therapy), or with compromised renal function, co-administration of NSAIDs, including selective COX-2 inhibitors, with ACE inhibitors, may result in deterioration of renal function, including possible acute renal failure. Discontinuation of NSAID therapy is usually followed by recovery to the pretreatment state.

Aspirin

When ARTHROTEC is administered with aspirin, the protein binding of diclofenac is reduced, although the clearance of the free ARTHROTEC is not altered. The clinical significance of this interaction is not known; however, as with other NSAIDs, concomitant administration of diclofenac sodium and aspirin is not generally recommended because of the potential risk of increased adverse effects.

Digoxin

Elevated digoxin levels have been reported in patients receiving digoxin and diclofenac sodium. Patients receiving digoxin and ARTHROTEC should be monitored for possible digoxin toxicity.

Warfarin

The effects of warfarin and NSAIDs on GI bleeding are synergistic, such that users of both drugs together have a risk of serious bleeding greater than users of either drug alone.

Oral hypoglycemics

Diclofenac sodium does not alter glucose metabolism in healthy people nor does it alter the effects of oral hypoglycemic agents. There are rare reports, however, from marketing experience, of changes in effects of insulin or oral hypoglycemic agents in the presence of diclofenac sodium that necessitated change in the doses of such agents. Both hypo- and hyperglycemic effects have been reported. A direct causal relationship has not been established, but physicians should consider the possibility that diclofenac sodium may alter a diabetic patient's response to insulin or oral hypoglycemic agents.

Methotrexate

NSAIDs have been reported to competitively inhibit methotrexate accumulation in rabbit kidney slices. This may indicate that they could enhance the toxicity of methotrexate. Caution should be used when NSAIDs are administered concomitantly with methotrexate.

Cyclosporine

ARTHROTEC, like other NSAID containing products, may affect renal prostaglandins and increase the toxicity of certain drugs. Ingestion of ARTHROTEC may increase cyclosporine nephrotoxicity. Patients who begin taking ARTHROTEC or who increase their dose of ARTHROTEC while taking cyclosporine may develop toxicity characteristic for cyclosporine. They should be observed closely, particularly if renal function is impaired.

Lithium

NSAIDs have produced an elevation of plasma lithium levels and a reduction in renal lithium clearance. The mean minimum lithium concentration increased 15% and the renal clearance was decreased by approximately 20%. These effects have been attributed to inhibition of renal prostaglandin synthesis by the NSAID. Thus, when NSAIDs and lithium are administered concurrently, subjects should be observed carefully for signs of lithium toxicity.

Antacids

Antacids reduce the bioavailability of misoprostol acid. Antacids may also delay absorption of diclofenac sodium. Magnesium-containing antacids exacerbate misoprostol-associated diarrhea. Thus, it is not recommended that ARTHROTEC be coadministered with magnesium-containing antacids.

Diuretics

Clinical studies, as well as postmarketing observations, have shown that ARTHROTEC can reduce the natriuretic effect of furosemide and thiazides in some patients. This response has been attributed to inhibition of renal prostaglandin synthesis. During concomitant therapy with NSAIDs, the patient should be observed closely for signs of renal failure (see WARNINGS, Renal Effects), as well as to assure diuretic efficacy. Concomitant therapy with potassium-sparing diuretics may be associated with increased serum potassium levels.

Voriconazole

In a published study, single dose diclofenac (50 mg) was coadministered with the last dose of voriconazole (400 mg every 12 hours on Day 1, followed by 200 mg every 12 hours on Day 2). The mean Cmax and AUC of diclofenac were increased by 2.1-fold and 1.8-fold respectively when coadministered with voriconazole compared to diclofenac alone.

Other drugs

In small groups of patients (7–10 patients/interaction study), the concomitant administration of azathioprine, gold, chloroquine, D-penicillamine, prednisolone, doxycycline, or digitoxin did not significantly affect the peak levels and AUC levels of diclofenac sodium. Phenobarbital toxicity has been reported to have occurred in a patient on chronic phenobarbital treatment following the initiation of diclofenac therapy. In vitro, diclofenac interferes minimally with the protein binding of prednisolone (10% decrease in binding). Benzylpenicillin, ampicillin, oxacillin, chlortetracycline, doxycycline, cephalothin, erythromycin, and sulfamethoxazole have no influence, in vitro, on the protein binding of diclofenac in human serum.

Animal toxicology

A reversible increase in the number of normal surface gastric epithelial cells occurred in the dog, rat, and mouse during long-term toxicology studies with misoprostol. No such increase has been observed in humans administered misoprostol for up to 1 year. An apparent response of the female mouse to misoprostol in long-term studies at 100 to 1000 times the human dose was hyperostosis, mainly of the medulla of sternebrae. Hyperostosis did not occur in long-term studies in the dog and rat and has not been seen in humans treated with misoprostol.

Carcinogenesis, mutagenesis, impairment of fertility

Long-term animal studies to evaluate the potential for carcinogenesis and animal studies to evaluate the effects on fertility have been performed with each component of ARTHROTEC given alone. ARTHROTEC itself (diclofenac sodium and misoprostol combinations in 250:1 ratio) was not genotoxic in the Ames test, the Chinese hamster ovary cell (CHO/HGPRT) forward mutation test, the rat lymphocyte chromosome aberration test, or the mouse micronucleus test.

In a 24-month rat carcinogenicity study, oral misoprostol at doses up to 2.4 mg/kg/day (14.4 mg/m^2/day, 24 times the recommended maximum human dose of 0.6 mg/m^2/day) was not tumorigenic. In a 21-month mouse carcinogenicity study, oral misoprostol at doses up to 16 mg/kg/day (48 mg/m^2/day), 80 times the recommended maximum human dose based on body surface area, was not tumorigenic. Misoprostol, when administered to male and female breeding rats in an oral dose range of 0.1 to 10 mg/kg/day (0.6 to 60 mg/m^2/day, 1 to 100 times the recommended maximum human dose based on body surface area) produced dose-related pre- and post-implantation losses and a significant decrease in the number of live pups born at the highest dose. These findings suggest the possibility of a general adverse effect on fertility in males and females.

In a 24-month rat carcinogenicity study, oral diclofenac sodium up to 2 mg/kg/day (12 mg/m^2/day) was not tumorigenic. For a 50-kg person of average height (1.46m^2 body surface area), this dose represents 0.08 times the recommended maximum human dose (148 mg/m^2) on a body surface area basis. In a 24-month mouse carcinogenicity study, oral diclofenac sodium at doses up to 0.3 mg/kg/day (0.9 mg/m^2/day, 0.006 times the recommended maximum human dose based on body surface area) in males and 1 mg/kg/day (3 mg/m^2/day, 0.02 times the recommended maximum human dose based on body surface area) in females was not tumorigenic. Diclofenac sodium at oral doses up to 4 mg/kg/day (24 mg/m^2/day, 0.16 times the recommended maximum human dose based on body surface area) was found to have no effect on fertility and reproductive performance of male and female rats.

Pregnancy

Pregnancy category X: See boxed CONTRAINDICATIONS AND WARNINGS regarding misoprostol.

Non-teratogenic effects

See boxed CONTRAINDICATIONS AND WARNINGS. Misoprostol may endanger pregnancy (may cause abortion) and thereby cause harm to the fetus when administered to a pregnant woman. Misoprostol may produce uterine contractions, uterine bleeding, and expulsion of the products of conception. Misoprostol has been used to ripen the cervix, to induce labor, and to treat postpartum hemorrhage, outside of its approved indication. A major adverse effect of these uses is hyperstimulation of the uterus. Uterine rupture, amniotic fluid embolism, severe genital bleeding, shock, fetal bradycardia, and fetal and material death have been reported. Higher doses of misoprostol, including the 100 mcg tablet, may increase the risk of complications from uterine hyperstimulation. ARTHROTEC, which contains 200 mcg of misoprostol, is likely to have a greater risk of uterine hyperstimulation than the 100 mcg tablet of misoprostol. Abortions caused by misoprostol may be incomplete. If a woman is or becomes pregnant while taking this drug, the drug should be discontinued and the patient apprised of the potential hazard to the fetus.

Cases of amniotic fluid embolism, which resulted in maternal and fetal death, have been reported with use of misoprostol during pregnancy. Severe vaginal bleeding, retained placenta, shock, fetal bradycardia, and pelvic pain have also been reported. These women were administered misoprostol vaginally and/or orally over a range of doses.

Additionally, because of the known effects of nonsteroidal anti-inflammatory drugs including the diclofenac sodium component of ARTHROTEC, on the fetal cardiovascular system (closure of ductus arteriosus), use during pregnancy (particularly late pregnancy) should be avoided.

Teratogenic effects

See boxed CONTRAINDICATIONS AND WARNINGS. Congenital anomalies sometimes associated with fetal death have been reported subsequent to the unsuccessful use of misoprostol as an abortifacient, but the drug's teratogenic mechanism has not been demonstrated. Several reports in the literature associate the use of misoprostol during the first trimester of pregnancy with skull defects, cranial nerve palsies, facial malformations, and limb defects.

An oral teratology study has been performed in pregnant rabbits at dose combinations (250:1 ratio) up to 10 mg/kg/day diclofenac sodium (120 mg/m^2/day, 0.8 times the recommended maximum human dose based on body surface area) and 0.04 mg/kg/day misoprostol (0.48 mg/m^2/day, 0.8 times the recommended maximum human dose based on body surface area) and has revealed no evidence of teratogenic potential for ARTHROTEC.

Oral teratology studies have been performed in pregnant rats at doses up to 1.6 mg/kg/day (9.6 mg/m^2/day, 16 times the recommended maximum human dose based on body surface area) and pregnant rabbits at doses up to 1.0 mg/kg/day (12 mg/m^2/day, 20 times the recommended maximum human dose based on body surface area) and have revealed no evidence of teratogenic potential for misoprostol.

Oral teratology studies have been performed in pregnant mice at doses up to 20 mg/kg/day (60 mg/m^2/day, 0.4 times the recommended maximum human dose based on body surface area), pregnant rats at doses up to 10 mg/kg/day (60 mg/m^2/day, 0.4 times the recommended maximum human dose based on body surface area) and pregnant rabbits at doses up to 10 mg/kg/day (120 mg/m^2/day, 0.8 times the recommended maximum human dose based on body surface area) and have revealed no evidence of teratogenic potential for diclofenac sodium.

However, animal reproduction studies are not always predictive of human response. There are no adequate and well-controlled studies in pregnant women.

Nursing mothers

Diclofenac sodium has been found in the milk of nursing mothers. Misoprostol is rapidly metabolized in the mother to misoprostol acid, which is biologically active and is excreted in breast milk. There are no published reports of adverse effects of misoprostol in breastfeeding infants of mothers taking misoprostol. Caution should be exercised when ARTHROTEC is administered to a nursing woman.

Labor and Delivery

In rat studies with NSAIDs, as with other drugs known to inhibit prostaglandin synthesis, an increased incidence of dystocia, delayed parturition, and decreased pup survival occurred.

Pediatric use

Safety and effectiveness of ARTHROTEC in pediatric patients have not been established.

Geriatric use

As with any NSAIDs, caution should be exercised in treating the elderly (65 years and older).

Of the more than 2,100 subjects in clinical studies with ARTHROTEC, 25% were 65 and over, while 6% were 75 and over. In studies with diclofenac, 31% of subjects were 65 and over. No overall differences in safety or effectiveness were observed between these subjects and younger subjects, and other reported clinical experience has not identified differences in responses between the elderly and younger patients, but greater sensitivity of some older individuals cannot be ruled out.

Diclofenac is known to be substantially excreted by the kidney, and the risk of toxic reactions to ARTHROTEC may be greater in patients with impaired renal function. Because elderly patients are more likely to have decreased renal function, care should be taken in dose selection, and it may be useful to monitor renal function (see WARNINGS—Renal Effects).

Based on studies in the elderly, no adjustment of the dose of ARTHROTEC is necessary in the elderly for pharmacokinetic reasons (see Pharmacokinetics of ARTHROTEC—Specific populations), although many elderly may need to receive a reduced dose because of low body weight or disorders associated with aging.

ADVERSE REACTIONS

Adverse reactions associated with ARTHROTEC

Adverse reaction information for ARTHROTEC is derived from Phase III multinational controlled clinical trials in over 2,000 patients receiving ARTHROTEC 50 or ARTHROTEC 75, as well as from blinded, controlled trials of Voltaren® Delayed-Release tablets (diclofenac) and Cytotec® tablets (misoprostol).

Gastrointestinal

GI disorders had the highest reported incidence of adverse events for patients receiving ARTHROTEC. These events were generally minor, but led to discontinuation of therapy in 9% of patients on ARTHROTEC and 5% of patients on diclofenac. For GI ulcer rates, see CLINICAL STUDIES—Upper gastrointestinal safety.

GI disorder | ARTHROTEC | Diclofenac
Abdominal pain | 21% | 15%
Diarrhea | 19% | 11%
Dyspepsia | 14% | 11%
Nausea | 11% | 6%
Flatulence | 9% | 4%

ARTHROTEC can cause more abdominal pain, diarrhea, and other GI symptoms than diclofenac alone.

Diarrhea and abdominal pain developed early in the course of therapy, and were usually self-limited (resolved after 2 to 7 days). Rare instances of profound diarrhea leading to severe dehydration have been reported in patients receiving misoprostol. Patients with an underlying condition such as inflammatory bowel disease, or those in whom dehydration, were it to occur, would be dangerous, should be monitored carefully if ARTHROTEC is prescribed. The incidence of diarrhea can be minimized by administering ARTHROTEC with food and by avoiding coadministration with magnesium-containing antacids.

Gynecological

Gynecological disorders previously reported with misoprostol use have also been reported for women receiving ARTHROTEC (see below). Postmenopausal vaginal bleeding may be related to administration of ARTHROTEC. If it occurs, diagnostic workup should be undertaken to rule out gynecological pathology (see boxed CONTRAINDICATIONS AND WARNINGS).

Elderly

Overall, there were no significant differences in the safety profile of ARTHROTEC in over 500 patients 65 years of age or older compared with younger patients.

Other adverse experiences reported occasionally or rarely with ARTHROTEC, diclofenac or other NSAIDs, or misoprostol are:

Body as a whole: Asthenia, death, fatigue, fever, infection, malaise, sepsis, chills.

Cardiovascular system: Arrhythmia, atrial fibrillation, congestive heart failure, hypertension, hypotension, increased CPK, increased LDH, myocardial infarction, palpitations, phlebitis, premature ventricular contractions, syncope, tachycardia, vasculitis.

Central and peripheral nervous system: Coma, convulsions, dizziness, drowsiness, headache, hyperesthesia, hypertonia, hypoesthesia, insomnia, meningitis, migraine, neuralgia, paresthesia, somnolence, stroke, tremor, vertigo.

Digestive: Anorexia, appetite changes, constipation, dry mouth, dysphagia, enteritis, esophageal ulceration, esophagitis, eructation, gastritis, gastroesophageal reflux, GI bleeding, GI neoplasm benign, glossitis, heartburn, hematemesis, hemorrhoids, intestinal perforation, peptic ulcer, stomatitis and ulcerative stomatitis, tenesmus, vomiting.

Female reproductive disorders: Breast pain, dysmenorrhea, intermenstrual bleeding, leukorrhea, menstrual disorder, menorrhagia, vaginal hemorrhage.

Hemic and lymphatic system: Agranulocytosis, anemia, aplastic anemia, coagulation time increased, ecchymosis, eosinophilia, epistaxis, hemolytic anemia, leukocytosis, leukopenia, lymphadenopathy, melena, pancytopenia, pulmonary embolism, purpura, rectal bleeding, thrombocythemia, thrombocytopenia.

Hypersensitivity: Angioedema, laryngeal/pharyngeal edema, urticaria.

Liver and biliary system: Abnormal hepatic function, bilirubinemia, hepatitis, jaundice, liver failure, pancreatitis.

Male reproductive disorders: Impotence, perineal pain.

Metabolic and nutritional: Alanine aminotransferase increased, alkaline phosphatase increased, aspartate aminotransferase increased, BUN increased, dehydration, glycosuria, gout, hypercholesterolemia, hyperglycemia, hyperuricemia, hypoglycemia, hyponatremia, periorbital edema, porphyria, weight changes.

Musculoskeletal system: Arthralgia, myalgia.

Psychiatric: Anxiety, concentration impaired, confusion, depression, disorientation, dream abnormalities, hallucinations, irritability, nervousness, paranoia, psychotic reaction.

Respiratory system: Asthma, coughing, dyspnea, hyperventilation, pneumonia, respiratory depression.

Skin and appendages: Acne, alopecia, bruising, eczema, erythema multiforme, exfoliative dermatitis, pemphigoid reaction, photosensitivity, pruritus, pruritus ani, rash, skin ulceration, Stevens-Johnson syndrome, sweating increased, toxic epidermal necrolysis.

Special senses: Hearing impairment, taste loss, taste perversion, tinnitus.

Urinary system: Cystitis, dysuria, hematuria, interstitial nephritis, micturition frequency, nocturia, nephrotic syndrome, oliguria/polyuria, papillary necrosis, proteinuria, renal failure, urinary tract infection.

Vision: Amblyopia, blurred vision, conjunctivitis, diplopia, glaucoma, iritis, lacrimation abnormal, night blindness, vision abnormal.

OVERDOSAGE

The toxic dose of ARTHROTEC has not been determined. However, signs of overdosage from the components of the product have been described.

Diclofenac sodium

Clinical signs that may suggest diclofenac sodium overdose include GI complaints, confusion, drowsiness, or general hypotonia. Reports of overdosage with diclofenac cover 66 cases. In approximately one-half of these reports of overdosage, concomitant medications were also taken. The highest dose of diclofenac was 5.0 g in a 17-year-old man who suffered loss of consciousness, increased intracranial pressure, and aspiration pneumonitis, and died 2 days after overdose. A 24-year-old woman who took 4.0 g and the 28- and 42-year-old women, each of whom took 3.75 g, did not develop any clinically significant signs or symptoms. However, there was a report of a 17-year-old woman who experienced vomiting and drowsiness after an overdose of 2.37 g of diclofenac.

Animal studies show a wide range of susceptibilities to acute overdosage, with primates being more resistant to acute toxicity than rodents (LD50 in mg/kg: rats, 55; dogs, 500; monkeys, 3200).

Misoprostol

The toxic dose of misoprostol in humans has not been determined. Cumulative total daily doses of 1600 mcg have been tolerated, with only symptoms of GI discomfort being reported. In animals, the acute toxic effects are diarrhea, GI lesions, focal cardiac necrosis, hepatic necrosis, renal tubular necrosis, testicular atrophy, respiratory difficulties, and depression of the central nervous system. Clinical signs that may indicate an overdose are sedation, tremor, convulsions, dyspnea, abdominal pain, diarrhea, fever, palpitations, hypotension, or bradycardia.

ARTHROTEC

Symptoms of overdosage with ARTHROTEC should be treated with supportive therapy. In case of acute overdosage, gastric lavage is recommended. Induced diuresis may be beneficial because diclofenac sodium and misoprostol metabolites are excreted in the urine. The effect of dialysis or hemoperfusion on the elimination of diclofenac sodium (99% protein bound) and misoprostol acid remains unproven. The use of oral activated charcoal may help to reduce the absorption of diclofenac sodium and misoprostol.

DOSAGE AND ADMINISTRATION

Carefully consider the potential benefits and risks of ARTHROTEC and other treatment options before deciding to use ARTHROTEC. Use the lowest effective dose for the shortest duration consistent with individual patient treatment goals (see WARNINGS).

After observing the response to initial therapy with ARTHROTEC, the dose and frequency should be adjusted to suit an individual patient's needs.

For the relief of rheumatoid arthritis and osteoarthritis, the recommended dose is given below.

ARTHROTEC is administered as ARTHROTEC 50 (50 mg diclofenac sodium/200 mcg misoprostol) or as ARTHROTEC 75 (75 mg diclofenac sodium/200 mcg misoprostol).

Note: See SPECIAL DOSING CONSIDERATIONS section below.

Osteoarthritis

The recommended dosage for maximal GI mucosal protection is ARTHROTEC 50 tid. For patients who experience intolerance, ARTHROTEC 75 bid or ARTHROTEC 50 bid can be used, but are less effective in preventing ulcers. This fixed combination product, ARTHROTEC, is not recommended for patients who would not receive the appropriate dose of both ingredients. Doses of the components delivered with these regimens are as follows:

 | OA regimen | Diclofenac sodium (mg/day) | Misoprostol (mcg/day)
ARTHROTEC 50 | tid | 150 | 600
 | bid | 100 | 400
ARTHROTEC 75 | bid | 150 | 400

Rheumatoid Arthritis

The recommended dosage is ARTHROTEC 50 tid or qid. For patients who experience intolerance, ARTHROTEC 75 bid or ARTHROTEC 50 bid can be used, but are less effective in preventing ulcers. This fixed combination product, ARTHROTEC, is not recommended for patients who would not receive the appropriate dose of both ingredients. Doses of the components delivered with these regimens are as follows:

 | RA regimen | Diclofenac sodium (mg/day) | Misoprostol (mcg/day)
ARTHROTEC 50 | qid | 200 | 800
 | tid | 150 | 600
 | bid | 100 | 400
ARTHROTEC 75 | bid | 150 | 400

SPECIAL DOSING CONSIDERATIONS

ARTHROTEC contains misoprostol, which provides protection against gastric and duodenal ulcers (see CLINICAL STUDIES). For gastric ulcer prevention, the 200 mcg qid and tid regimens are therapeutically equivalent, but more protective than the bid regimen. For duodenal ulcer prevention, the qid regimen is more protective than the tid or bid regimens. However, the qid regimen is less well tolerated than the tid regimen because of usually self-limited diarrhea related to the misoprostol dose (see ADVERSE REACTIONS —Gastrointestinal), and the bid regimen may be better tolerated than tid in some patients.

Dosages may be individualized using the separate products (misoprostol and diclofenac), after which the patient may be changed to the appropriate dose of ARTHROTEC. If clinically indicated, misoprostol co-therapy with ARTHROTEC, or use of the individual components to optimize the misoprostol dose and/or frequency of administration, may be appropriate. The total dose of misoprostol should not exceed 800 mcg/day, and no more than 200 mcg of misoprostol should be administered at any one time. Doses of diclofenac higher than 150 mg/day in osteoarthritis or higher than 225 mg/day in rheumatoid arthritis are not recommended.

For additional information, it may be helpful to refer to the package inserts for Cytotec® tablets and Voltaren® tablets.

HOW SUPPLIED

ARTHROTEC (diclofenac sodium/misoprostol) is supplied as a film-coated tablet in dosage strength 75 mg diclofenac sodium/200 mcg misoprostol.

The 75 mg/200 mcg dosage strength is a round, biconvex, white to off-white tablet imprinted with four "A's" encircling a "75" in the middle on one side and "SEARLE" and "1421" on the other.

The dosage strengths are supplied in:

Bottles of 30: NDC 16590-024-30

Bottles of 60: NDC 16590-024-60

STORAGE AND HANDLING

Store at or below 25°C (77°F), in a dry area.

Relabeling and Repackaging by:
STAT Rx USA LLC
Gainesville, GA 30501

PATIENT INFORMATION

Read this leaflet before taking ARTHROTEC (diclofenac sodium 50 or 75 mg/misoprostol 200 mcg) and each time your prescription is renewed because the leaflet may be changed.

ARTHROTEC is being prescribed by your doctor for treatment of your arthritis symptoms while at the same time providing protection from the development of stomach and intestinal ulcers due to the arthritis medication. ARTHROTEC contains diclofenac, an arthritis medication. ARTHROTEC also contains misoprostol to decrease the chance of getting stomach and intestinal ulcers that sometimes develop with NSAID medications. Serious side effects are still possible, however, and you should report to your doctor any signs or symptoms of gastrointestinal ulceration or bleeding, skin rash, weight gain or swelling. If signs of liver toxicity occur (nausea, fatigue, lethargy, itching, jaundice, right upper quadrant tenderness, and "flu-like" symptoms), you should stop therapy and seek immediate medical attention.

If signs of an anaphylactic reaction occur (e.g., difficulty breathing, swelling of the face or throat), you should stop therapy and seek immediate medical attention (see WARNINGS).

Do not take ARTHROTEC if you are pregnant (see boxed CONTRAINDICATIONS AND WARNINGS). ARTHROTEC contains diclofenac sodium and misoprostol. Misoprostol can cause abortion (sometimes incomplete which could lead to dangerous bleeding and require hospitalization and surgery), premature birth, or birth defects. It is also important to avoid pregnancy while taking this medication and for at least one month or through one menstrual cycle after you stop taking it. Misoprostol has been reported to cause the uterus to rupture (tear) when given after the eighth week of pregnancy. Rupture (tearing) of the uterus can result in severe bleeding, hysterectomy, and/or maternal or fetal death.

If you become pregnant during therapy with ARTHROTEC, stop taking ARTHROTEC and contact your doctor immediately. Remember that even if you are using a means of birth control, it is still possible to become pregnant. Should this occur, stop taking ARTHROTEC and consult your doctor immediately.

ARTHROTEC is not recommended for nursing mothers.

ARTHROTEC, like other NSAIDs, may cause an increased risk of heart attack or stroke, which can lead to death. This risk may increase with duration of use. If you have heart disease or risk factors for heart disease, you may be at greater risk (see boxed CONTRAINDICATIONS AND WARNINGS). ARTHROTEC should never be used for treatment of peri-operative pain in the setting of coronary artery bypass graft (CABG) surgery (see boxed CONTRAINDICATIONS AND WARNINGS).

Although serious CV events can occur without warning symptoms, ask for medical advice when observing signs and symptoms of chest pain, shortness of breath, weakness, or slurring of speech (see boxed CONTRAINDICATIONS AND WARNINGS).

ARTHROTEC, like other NSAIDs, may cause GI discomfort and, rarely, serious GI effects such as ulcers and bleeding, which may result in hospitalization and even death.

ARTHROTEC may cause diarrhea, abdominal pain, upset stomach, and/or nausea in some people. In most cases these problems develop during the first few weeks of therapy and stop after about a week with continued treatment. You can minimize possible diarrhea by making sure you take ARTHROTEC with meals and by avoiding the use of antacids containing magnesium (if needed, use one containing aluminum or calcium instead). ARTHROTEC tablets should be swallowed whole and not chewed, crushed, or dissolved.

Because these side effects are usually mild to moderate and usually go away in a matter of days, most patients can continue to take ARTHROTEC. If you have prolonged difficulty (more than 7 days), or if you have severe diarrhea, cramping, and/or nausea, call your doctor.

ARTHROTEC may also cause serious gastrointestinal (GI) adverse events including inflammation, bleeding, ulceration, and perforation of the stomach, small intestine, or large intestine, which can lead to death. These events can occur at any time during use and without warning symptoms. Elderly patients are at greater risk for serious gastrointestinal events (see boxed CONTRAINDICATIONS AND WARNINGS). This risk may increase with duration of use.

Although serious GI tract ulcerations and bleeding can occur without warning symptoms, ask for medical advice when observing signs and symptoms of ulceration and bleeding, including epigastric pain, dyspepsia, melena, and hematemesis.

(See boxed CONTRAINDICATIONS AND WARNINGS.)

ARTHROTEC, like other NSAIDs, may cause serious skin side effects, such as exfoliative dermatitis, Stevens-Johnson Syndrome (SJS), and toxic epidermal necrolysis, which may result in hospitalization and even death.

Although serious skin reactions may occur without warning, ask for medical advice when observing signs or symptoms, such as skin rash and blisters, fever, or other signs of hypersensitivity such as itching. Stop the drug immediately at the first appearance of skin rash or any other signs of hypersensitivity and contact your physician as soon as possible.

Take ARTHROTEC only according to the directions given by your doctor. Changes in dose should be made only with your doctor's approval.

Do not give ARTHROTEC to anyone else. It has been prescribed for your specific condition, may not be the correct treatment for another person, and could be dangerous for another person, especially a woman who may be, or could become, pregnant.

This information sheet does not cover all possible side effects of ARTHROTEC. See your doctor if you have questions.

Keep out of reach of children.

Rx only

LAB-0061-18.0
April 2012

Medication Guide for Non-Steroidal Anti-Inflammatory Drugs (NSAIDs)

(See the end of this Medication Guide for a list of prescription NSAID medicines.)

What is the most important information I should know about medicines called Non-Steroidal Anti-Inflammatory Drugs (NSAIDs)?

NSAID medicines may increase the chance of a heart attack or stroke that can lead to death. This chance increases:

- with longer use of NSAID medicines
- in people who have heart disease

NSAID medicines should never be used right before or after a heart surgery called a "coronary artery bypass graft (CABG)."

NSAID medicines can cause ulcers and bleeding in the stomach and intestines at any time during treatment. Ulcers and bleeding:

- can happen without warning symptoms
- may cause death

The chance of a person getting an ulcer or bleeding increases with:

- taking medicines called "corticosteroids" and "anticoagulants"
- longer use
- smoking
- drinking alcohol
- older age
- having poor health

NSAID medicines should only be used:

- exactly as prescribed
- at the lowest dose possible for your treatment
- for the shortest time needed

What are Non-Steroidal Anti-Inflammatory Drugs (NSAIDs)?

NSAID medicines are used to treat pain and redness, swelling, and heat (inflammation) from medical conditions such as:

- different types of arthritis
- menstrual cramps and other types of short-term pain

Who should not take a Non-Steroidal Anti-Inflammatory Drug (NSAID)?

Do not take an NSAID medicine:

- if you had an asthma attack, hives, or other allergic reaction with aspirin or any other NSAID medicine
- for pain right before or after heart bypass surgery

Tell your healthcare provider:

- about all of your medical conditions.
- about all of the medicines you take. NSAIDs and some other medicines can interact with each other and cause serious side effects. Keep a list of your medicines to show to your healthcare provider and pharmacist.
- if you are pregnant. NSAID medicines should not be used by pregnant women late in their pregnancy.
- if you are breastfeeding. Talk to your doctor.

What are the possible side effects of Non-Steroidal Anti-Inflammatory Drugs (NSAIDs)?

Serious side effects include:

- heart attack
- stroke
- high blood pressure
- heart failure from body swelling (fluid retention)
- kidney problems including kidney failure
- bleeding and ulcers in the stomach and intestine
- low red blood cells (anemia)
- life-threatening skin reactions
- life-threatening allergic reactions
- liver problems including liver failure
- asthma attacks in people who have asthma

Other side effects include:

- stomach pain
- constipation
- diarrhea
- gas
- heartburn
- nausea
- vomiting
- dizziness

Get emergency help right away if you have any of the following symptoms:

- shortness of breath or trouble breathing
- chest pain
- weakness in one part or side of your body

- slurred speech
- swelling of the face or throat

Stop your NSAID medicine and call your healthcare provider right away if you have any of the following symptoms:

- nausea
- more tired or weaker than usual
- itching
- your skin or eyes look yellow
- stomach pain
- flu-like symptoms

- vomit blood
- there is blood in your bowel movement or it is black and sticky like tar
- skin rash or blisters with fever
- unusual weight gain
- swelling of the arms and legs, hands and feet

These are not all the side effects with NSAID medicines. Talk to your healthcare provider or pharmacist for more information about NSAID medicines.

Call your doctor for medical advice about side effects. You may report side effects to FDA at 1-800-FDA-1088.

Other information about Non-Steroidal Anti-Inflammatory Drugs (NSAIDs)

- Aspirin is an NSAID medicine but it does not increase the chance of a heart attack. Aspirin can cause bleeding in the brain, stomach, and intestines. Aspirin can also cause ulcers in the stomach and intestines.
- Some of these NSAID medicines are sold in lower doses without a prescription (over –the –counter). Talk to your healthcare provider before using over –the –counter NSAIDs for more than 10 days.

NSAID medicines that need a prescription

Generic Name | Tradename
Celecoxib | Celebrex
Diclofenac | Cataflam, Voltaren, Arthrotec (combined with misoprostol)
Diflunisal | Dolobid
Etodolac | Lodine, Lodine XL
Fenoprofen | Nalfon, Nalfon 200
Flurbiprofen | Ansaid
Ibuprofen | Motrin, Tab-Profen, Vicoprofen [Vicoprofen contains the same dose of ibuprofen as over-the-counter (OTC) NSAIDs, and is usually used for less than 10 days to treat pain. The OTC NSAID label warns that long term continuous use may increase the risk of heart attack or stroke.] (combined with hydrocodone), Combunox (combined with oxycodone)
Indomethacin | Indocin, Indocin SR, Indo-Lemmon, Indomethagan
Ketoprofen | Oruvail
Ketorolac | Toradol
Mefenamic Acid | Ponstel
Meloxicam | Mobic
Nabumetone | Relafen
Naproxen | Naprosyn, Anaprox, Anaprox DS, EC-Naproxyn, Naprelan, Naprapac (copackaged with lansoprazole)
Oxaprozin | Daypro
Piroxicam | Feldene
Sulindac | Clinoril
Tolmetin | Tolectin, Tolectin DS, Tolectin 600

This Medication Guide has been approved by the U.S. Food and Drug Administration.

LAB-0609-1.0

PRINCIPAL DISPLAY PANEL - ARTHROTEC 75mg /200mcg Tablets

Arthrotec® 75

75 mg Diclofenac Sodium / 200 mcg Misoprostol

Distributed by
G.D. Searle LLC
Division of Pfizer Inc, NY, NY 10017

Relabeling and Repackaging by:
STAT Rx USA LLC
Gainesville, GA 30501